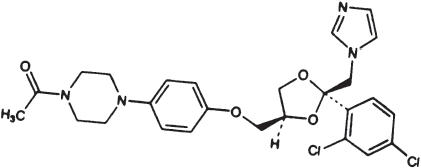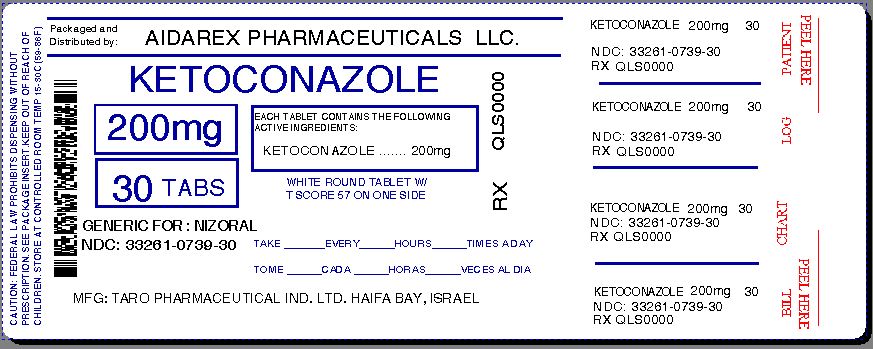 DRUG LABEL: Ketoconazole
NDC: 33261-739 | Form: TABLET
Manufacturer: Aidarex Pharmaceuticals LLC
Category: prescription | Type: HUMAN PRESCRIPTION DRUG LABEL
Date: 20140105

ACTIVE INGREDIENTS: KETOCONAZOLE 200 mg/1 1
INACTIVE INGREDIENTS: SILICON DIOXIDE; STARCH, CORN; LACTOSE MONOHYDRATE; MAGNESIUM STEARATE; CELLULOSE, MICROCRYSTALLINE; POVIDONES

Ketoconazole
Tablets USP,
200 MG

Rx only

WARNING

Ketoconazole tablets USP, 200 mg should be used only when other effective antifungal therapy is not available or tolerated and the potential benefits are considered to outweigh the potential risks.

Hepatotoxicity

Serious hepatotoxicity, including cases with a fatal outcome or requiring liver transplantation has occurred with the use of oral ketoconazole. Some patients had no obvious risk factors for liver disease. Patients receiving this drug should be informed by the physician of the risk and should be closely monitored. See WARNINGS section.

QT Prolongation and Drug Interactions Leading to QT Prolongation

Co-administration of the following drugs with ketoconazole is contraindicated: dofetilide, quinidine, pimozide, cisapride. Ketoconazole can cause elevated plasma concentrations of these drugs and may prolong QT intervals, sometimes resulting in life-threatening ventricular dysrhythmias such as torsades de pointes. See CONTRAINDICATIONS, WARNINGS, and PRECAUTIONS: Drug Interactions sections.

DESCRIPTION

Ketoconazole tablets USP is a synthetic broad-spectrum antifungal agent available in scored white tablets, each containing 200 mg ketoconazole base for oral administration. Inactive ingredients are colloidal silicon dioxide, corn starch, lactose monohydrate, magnesium stearate, microcrystalline cellulose, and povidone. Ketoconazole is cis-1-acetyl-4-[4-[[2-(2,4dichlorophenyl)-2-(1H-imidazol-1-ylmethyl)-1,3-dioxolan-4-yl]methoxyl]phenyl] piperazine and has the following structural formula:

Ketoconazole is a white to slightly beige, odorless powder, soluble in acids, with a molecular weight of 531.44.

CLINICAL PHARMACOLOGY

Pharmacokinetics

Mean peak plasma levels of approximately 3.5 µg/mL are reached within 1 to 2 hours, following oral administration of a single 200 mg dose taken with a meal. Subsequent plasma elimination is biphasic with a half-life of 2 hours during the first 10 hours and 8 hours thereafter. Following absorption from the gastrointestinal tract, ketoconazole is converted into several inactive metabolites. The major identified metabolic pathways are oxidation and degradation of the imidazole and piperazine rings, oxidative Odealkylation and aromatic hydroxylation. About 13% of the dose is excreted in the urine, of which 2 to 4% is unchanged drug. The major route of excretion is through the bile into the intestinal tract. In vitro, the plasma protein binding is about 99% mainly to the albumin fraction. Only a negligible proportion of ketoconazole reaches the cerebrospinal fluid. Ketoconazole is a weak dibasic agent and thus requires acidity for dissolution and absorption.

Electrocardiogram

Pre-clinical electrophysiological studies have shown that ketoconazole inhibits the rapidly activating component of the cardiac delayed rectifier potassium current, prolongs the action potential duration, and may prolong the QTc interval. Data from some clinical PK/PD studies and drug interaction studies suggest that oral dosing with ketoconazole at 200 mg twice daily for 3 to 7 days can result in an increase of the QTc interval: a mean maximum increase of about 6 to 12 msec was seen at ketoconazole peak plasma concentrations about 1 to 4 hours after ketoconazole administration.

MICROBIOLOGY

Mechanism of Action

Ketoconazole blocks the synthesis of ergosterol, a key component of the fungal cell membrane, through the inhibition of cytochrome P-450 dependent enzyme lanosterol 14α-demethylase responsible for the conversion of lanosterol to ergosterol in the fungal cell membrane. This results in an accumulation of methylated sterol precursors and a depletion of ergosterol within the cell membrane thus weakening the structure and function of the fungal cell membrane.

Activity In Vitro & In Vivo

Ketoconazole tablets USP, 200 mg are active against clinical infections with Blastomyces dermatitidis, Coccidioides immitis, Histoplasma capsulatum, Paracoccidioides brasiliensis.

INDICATIONS AND USAGE

Ketoconazole tablets USP, 200 mg should be used only when other effective antifungal therapy is not available or tolerated and the potential benefits are considered to outweigh the potential risks.

Ketoconazole tablets USP, 200 mg are indicated for the treatment of the following systemic fungal infections in patients who have failed or who are intolerant to other therapies: blastomycosis, coccidioidomycosis, histoplasmosis, chromomycosis, and paracoccidioidomycosis. Ketoconazole tablets USP, 200 mg should not be used for fungal meningitis because it penetrates poorly into the cerebrospinal fluid.

CONTRAINDICATIONS

Drug Interactions

Coadministration of a number of CYP3A4 substrates is contraindicated with ketoconazole tablets. Coadministration with ketoconazole can cause elevated plasma concentrations of these drugs and may increase or prolong both therapeutic and adverse effects. For example, increased plasma concentrations of some of these drugs can lead to QT prolongation and ventricular tachyarrhythmias including occurrences of torsades de pointes, a potentially fatal arrhythmia. See WARNINGS section, and PRECAUTIONS: Drug Interactions section for specific examples.

Liver Disease

The use of ketoconazole tablets is contraindicated in patients with acute or chronic liver disease.

Hypersensitivity

Ketoconazole tablets USP, 200 mg is contraindicated in patients who have shown hypersensitivity to the drug.

WARNINGS

Ketoconazole tablets USP, 200 mg should be used only when other effective antifungal therapy is not available or tolerated and the potential benefits are considered to outweigh the potential risks.

Hepatotoxicity

Serious hepatotoxicity, including cases with a fatal outcome or requiring liver transplantation, has occurred with the use of oral ketoconazole. Some patients had no obvious risk factors for liver disease. Serious hepatotoxicity was reported both by patients receiving high doses for short treatment durations and by patients receiving low doses for long durations.

The hepatic injury has usually, but not always, been reversible upon discontinuation of ketoconazole tablets treatment. Cases of hepatitis have been reported in children.

At baseline, obtain laboratory tests (such as SGGT, alkaline phosphatase, ALT, AST, total bilirubin (TBL), Prothrombin Time (PT), International Normalization Ratio (INR), and testing for viral hepatitides). Patients should be advised against alcohol consumption while on treatment. If possible, use of other potentially hepatotoxic drugs should be avoided in patients receiving ketoconazole tablets.

Prompt recognition of liver injury is essential. During the course of treatment, serum ALT should be monitored weekly for the duration of treatment. If ALT values increase to a level above the upper limit of normal or 30 percent above baseline, or if the patient develops symptoms, ketoconazole treatment should be interrupted and a full set of liver tests should be obtained. Liver tests should be repeated to ensure normalization of values. Hepatotoxicity has been reported with restarting oral ketoconazole (rechallenge). If it is decided to restart oral ketoconazole, monitor the patient frequently to detect any recurring liver injury from the drug.

QT Prolongation and Drug Interactions Leading to QT Prolongation

Ketoconazole can prolong the QT interval. Co-administration of the following drugs with ketoconazole is contraindicated: dofetilide, quinidine, pimozide, and cisapride. Ketoconazole can cause elevated plasma concentrations of these drugs which may prolong the QT interval, sometimes resulting in life-threatening ventricular dysrhythmias such as torsades de pointes.

Adrenal Insufficiency

Ketoconazole tablets decrease adrenal corticosteroid secretion at doses of 400 mg and higher. This effect is not shared with other azoles. The recommended dose of 200 mg to 400 mg daily should not be exceeded.

Adrenal function should be monitored in patients with adrenal insufficiency or with borderline adrenal function and in patients under prolonged periods of stress (major surgery, intensive care, etc.).

Adverse Reactions Associated with Unapproved Uses

Ketoconazole has been used in high doses for the treatment of advanced prostate cancer and for Cushing's syndrome when other treatment options have failed. The safety and effectiveness of ketoconazole have not been established in these settings and the use of ketoconazole for these indications is not approved by FDA.

In a clinical trial involving 350 patients with metastatic prostatic cancer, eleven deaths were reported within two weeks of starting treatment with high doses of ketoconazole tablets (1200 mg/day). It is not possible to ascertain from the information available whether death was related to ketoconazole therapy or adrenal insufficiency in these patients with serious underlying disease.

Hypersensitivity

Anaphylaxis has been reported after the first dose. Several cases of hypersensitivity reactions including urticaria have also been reported.

Enhanced Sedation

Co-administration of ketoconazole tablets with oral midazolam, oral triazolam or alprazolam has resulted in elevated plasma concentrations of these drugs. This may potentiate and prolong hypnotic and sedative effects, especially with repeated dosing or chronic administration of these agents. Concomitant administration of ketoconazole tablets with oral triazolam, oral midazolam, or alprazolam is contraindicated. (See CONTRAINDICATIONS and PRECAUTIONS: Drug Interactions sections.)

Myopathy

Co-administration of CYP3A4 metabolized HMG-CoA reductase inhibitors such as simvastatin, and lovastatin is contraindicated with ketoconazole tablets. (See CONTRAINDICATIONS and PRECAUTIONS: Drug Interactions sections.)

PRECAUTIONS

General

Ketoconazole tablets have been demonstrated to lower serum testosterone. Once therapy with ketoconazole tablets has been discontinued, serum testosterone levels return to baseline values. Testosterone levels are impaired with doses of 800 mg per day and abolished by 1600 mg per day. Clinical manifestations of decreased testosterone concentrations may include gynecomastia, impotence and oligospermia.

Information for Patients

Patients should be instructed to report any signs and symptoms which may suggest liver dysfunction so that appropriate biochemical testing can be done. Such signs and symptoms may include unusual fatigue, anorexia, nausea and/or vomiting, abdominal pain, jaundice, dark urine or pale stools (see WARNINGS section).

Drug Interactions

Drugs that affect the absorption, distribution, metabolism, and excretion of ketoconazole may alter the plasma concentrations of ketoconazole. For example, gastric acid suppressants (e.g., antacids, histamine H2-blockers, proton pump inhibitors) have been shown to reduce plasma concentrations of ketoconazole.Ketoconazole is a substrate and potent inhibitor of CYP3A4. Therefore, the following drug interactions may occur when ketoconazole is co-administered with other drugs that interact with CYP3A4. (See Table 1 and Table 2 for an overview of these drug interactions; details are provided in the text that follows these tables.)

- Ketoconazole may decrease the elimination of drugs metabolized by CYP3A4, thereby increasing their plasma concentrations. Increased exposure to these drugs may cause an increase or prolongation of their therapeutic and/or adverse effects. Concomitant use with ketoconazole tablets is contraindicated for drugs known to present a risk of serious side effects with increased exposure (see BOXED WARNING, CONTRAINDICATIONS section, and PRECAUTIONS: Drug Interactions, Table 1). For others, monitoring of plasma concentrations is advised when possible. Clinical signs and symptoms associated with these drugs should be monitored, with dosage adjusted as needed.
- Inducers of CYP3A4 may decrease the plasma concentrations of ketoconazole (see Table 2). Ketoconazole may not be effective in patients concomitantly taking one of these drugs. Therefore, administration of these drugs with ketoconazole is not recommended.
- Other inhibitors of CYP3A4 may increase the plasma concentrations of ketoconazole (see Table 2). Patients who must take ketoconazole concomitantly with one of these drugs should be monitored closely for signs or symptoms of increased or prolonged pharmacologic effects of ketoconazole.

Table 1. Selected Drugs That Have Been Shown To or Are Predicted To Have Their Plasma Concentrations Altered By Ketoconazole [This list is not all-inclusive.]
Systemic exposure to these drugs is increased significantly by the addition of ketoconazole: Concomitant use with ketoconazole is contraindicated.
Alprazolam, midazolam, triazolam | HMG-CoA reductase inhibitors (lovastatin, simvastatin)
Cisapride | Nisoldipine
Dofetilide | Pimozide
Eplerenone | Quinidine
Ergot alkaloids (ergotamine, dihydroergotamine)
Systemic exposure to these drugs is increased by ketoconazole: Careful monitoring, with possible adjustment in dosage, is recommended.
Alfentanil, fentanyl, sulfentanil | Indinavir, saquinavir
Amlodipine, felodipine, nicardipine, nifedipine | Methylprednisolone
Bosentan | Rifabutin
Buspirone | Sildenafil
Busulfan | Sirolimus (co-administration not recommended)
Carbamazepine | Tacrolimus
Cilostazol | Telithromycin
Cyclosporine | Tolterodine
Digoxin | Trimetrexate
Docetaxel, paclitaxel | Verapamil
Oral anti-coagulants | Vinca alkaloids (vincristine, - vinblastine, vinorelbine)

Table 2. Selected Drugs That Have Been Shown To or Are Predicted To Alter The Plasma Concentration Of Ketoconazole
Systemic exposure to ketoconazole is reduced significantly by these drugs: Concomitant use with ketoconazole is not recommended.
Carbamazepine | Phenytoin
Gastric Acid Suppressants (antacids, antimuscarinics, histamine H2-blockers, proton pump inhibitors, sucralfate) | Rifampin, rifabutin, isoniazid
Nevirapine
Systemic exposure to ketoconazole is increased significantly by this drug: Dose reduction of ketoconazole should be considered
Ritonavir
*This list is not all-inclusive.

1. Effects of ketoconazole on other drugs

1.1 Systemic exposure to the following drugs is significantly increased by coadministration of ketoconazole. Concomitant use of these drugs with ketoconazole tablets USP, 200 mg is contraindicated

Alprazolam, midazolam, triazolam

Co-administration of ketoconazole tablets with alprazolam, midazolam, or triazolam has resulted in elevated plasma concentrations of these drugs. This may potentiate and prolong hypnotic and sedative effects, especially with repeated or chronic administration of these agents. Concomitant administration of ketoconazole tablets with alprazolam, oral midazolam, and oral triazolam is contraindicated. (See CONTRAINDICATIONS and WARNINGS sections.) Special precaution and patient monitoring are required with concomitant parenteral midazolam, because the sedative effect may be prolonged.

Cisapride

Oral ketoconazole potently inhibits the metabolism of cisapride resulting in a mean eight-fold increase in AUC of cisapride, which can lead to prolongation of QT interval. Therefore concomitant administration of ketaconazole tablets with cisapride is contraindicated. (See BOXED WARNING, CONTRAINDICATIONS, and WARNINGS sections.)

Dofetilide

The class III antiarrhythmic dofetilide is known to prolong the QT interval. The potential increase in dofetilide plasma concentrations when administered concomitantly with ketoconazole could result in serious cardiovascular events including QTc prolongation and rare occurrences of torsades de pointes. Therefore, concomitant administration of ketoconazole tablets with dofetilide is contraindicated. (See BOXED WARNING, CONTRAINDICATIONS, and WARNINGS sections.)

Eplerenone

Ketoconazole increases the eplerenone AUC by roughly 5-fold, thereby increasing the risk for hyperkalemia and hypotension. Co-administration of ketoconazole and eplerenone is contraindicated. (See CONTRAINDICATIONS section.)

Ergot Alkaloids

Elevated concentrations of ergot alkaloids can cause ergotism, i.e., a risk for vasospasm potentially leading to cerebral ischemia and/or ischemia of the extremities. Concomitant administration of ergot alkaloids such as dihydroergotamine and ergotamine with ketoconazole tablets is contraindicated. (See CONTRAINDICATIONS section.)

HMG-CoA Enzyme Inhibitors (lovastatin, simvastatin)

Co-administration of ketoconazole with CYP3A4-metabolized HMG-CoA reductase inhibitors such as simvastatin, and lovastatin, may increase the risk of skeletal muscle toxicity, including rhabdomyolysis. Concomitant administration of ketoconazole tablets with these HMG-CoA reductase inhibitors is contraindicated. (See CONTRAINDICATIONS and WARNINGS sections.)

Nisoldipine

Pre-treatment with and concomitant administration of ketoconazole resulted in a 24-fold and 11-fold increase in mean AUC and Cmax of nisoldipine, respectively, compared with treatment with nisoldipine 5 mg alone. Concomitant administration of ketoconazole with nisoldipine is contraindicated. (See CONTRAINDICATIONS section.)

Pimozide

Pimozide is known to prolong the QT interval and is partially metabolized by CYP3A4. Co-administration of ketoconazole and pimozide could result in serious cardiovascular events including QTc prolongation and rare occurrences of torsades de pointes, and is therefore contraindicated. (See BOXED WARNING, CONTRAINDICATIONS, and WARNINGS sections.)

Quinidine

The class IA antiarhythmic quinidine is known to prolong the QT interval. The potential increase in quinidine plasma concentrations when administered concomitantly with ketoconazole could result in serious cardiovascular events including QTc prolongation and rare occurrences of torsades de pointes. Therefore, concomitant administration of ketoconazole tablets with quinidine is contraindicated. (See BOXED WARNING, CONTRAINDICATIONS, and WARNINGS sections.)

1.2 Co-administration of ketoconazole with the following agents was shown or is expected to result in increased exposure to these drugs. Therefore, careful monitoring of plasma concentrations or adverse events of these drugs is recommended. Adjustment of dosage of these drugs may be needed

Alfentanil, sufentanil, fentanyl

In vitro data suggest that alfentanil, sufentanil and fentanyl are metabolized by CYP3A4. Concomitant administration of ketoconazole tablets and alfentanil, sufentanil, or fentanyl may increase plasma concentrations of the latter drugs.

Amlodipine, felodipine, nicardipine, nifedipine

CYP3A4 metabolized calcium channel blockers such as amlodipine, felodipine, nicardipine, and nifedipine should be used cautiously with ketoconazole tablets as ketoconazole may cause several-fold increases in plasma concentrations of these calcium channel blockers.

Bosentan

Concomitant administration of ketoconazole increased the Cmax and AUC of bosentan 2.1- and 2.3 – fold, respectively. No dosage adjustment of bosentan is needed but close monitoring for increased bosentan-associated adverse effects is recommended.

Buspirone

Concomitant administration of buspirone with ketoconazole may result in significant increases in plasma concentrations of buspirone. When administered with ketoconazole tablets, a low initial dose of buspirone with subsequent dosage adjustment based on clinical assessment is recommended.

Busulfan

Ketoconazole tablets may decrease the clearance and thus increase the systemic exposure to busulfan.

Carbamazepine

In vivo studies have demonstrated an increase in plasma carbamazepine concentrations in subjects concomitantly receiving ketoconazole. Close monitoring of plasma carbamazepine concentrations is recommended whenever ketoconazole is given to patients stabilized on carbamazepine therapy.

Cilostazol

Ketoconazole had been shown to increase both cilostazol AUC and Cmax by about two-fold when administered concurrently. Co-administration of ketoconazole with cilostazol resulted in increased incidences of adverse effects, such as headache. When ketoconazole tablets is administered concomitantly with cilostazol, the prescriber should consider up to a 50% reduction in cilostazol dosage.

Cyclosporine

Ketoconazole tablets may alter the metabolism of cyclosporine, thereby resulting in elevated cyclosporine plasma concentrations. Dosage adjustment may be required if cyclosporine or tacrolimus is given concomitantly with ketoconazole tablets.

Digoxin

Rare cases of elevated plasma concentrations of digoxin have been reported. It is not clear whether this was due to the combination of therapy. It is, therefore, advisable to monitor digoxin concentrations in patients receiving ketoconazole.

Docetaxel

In the presence of ketoconazole, the clearance of docetaxel in cancer patients was shown to decrease by 50%. When docetaxel and ketoconazole are administered together, dosage reduction in docetaxel may be necessary in order to minimize the incidence of toxicities associated with docetaxel.

Indinavir, saquinavir

Concomitant administration of ketoconazole and protease inhibitors metabolized by CYP3A4, such as indinavir and saquinavir, may increase plasma concentrations of these protease inhibitors. Dosage reduction of indinavir is recommended when administering ketoconazole concomitantly. No dosage adjustments are recommended when saquinavir and ketoconazole are coadministered for a short period of time.

Methylprednisolone

Ketoconazole tablets may alter the metabolism of methylprednisolone, resulting in elevated plasma concentrations of methylprednisolone. Dose adjustments may be required if methylprednisolone is given concomitantly with ketoconazole tablets.

Oral anti-coagulants

Oral imidazole compounds such as ketoconazole may enhance the anticoagulant effect of coumarin-like drugs, thus the anticoagulant effect should be carefully titrated and monitored.

Oral hypoglycemic agents

Because severe hypoglycemia has been reported in patients concomitantly receiving oral miconazole (an imidazole) and oral hypoglycemic agents, such a potential interaction involving the latter agents when used concomitantly with ketoconazole tablets (an imidazole) cannot be ruled out.

Rifabutin

Ketoconazole was shown to inhibit the CYP-mediated metabolism of rifabutin in vitro. Co-administration with ketoconazole tablets may result in elevated plasma concentrations of rifabutin.

Sildenafil

Ketoconazole had been shown to increase sildenafil plasma concentrations. When used concomitantly with ketoconazole tablets, a 50% reduction in sildenafil starting dose should be considered.

Sirolimus

Multiple-dose ketoconazole had been shown to increase sirolimus Cmax and AUC by 4.3-fold and 10.9-fold, respectively. The concomitant use of ketoconazole tablets and sirolimus is not recommended.

Tacrolimus

Ketoconazole had been shown to decrease the oral clearance of tacrolimus thereby leading to a 2-fold increase in tacrolimus oral bioavailability. Adjustment in tacrolimus dosage may be required if tacrolimus is given concomitantly with ketoconazole tablets.

Telithromycin

Ketoconazole increased the AUC of telithromycin by 1.5 to 2-fold. Use caution when administering telithromycin concurrently with ketoconazole tablets since this may result in an increased risk for telithromycin associated adverse events.

Tolterodine

In the presence of ketoconazole, the apparent oral clearance of tolterodine decreased resulting in at least a two-fold increase in tolterodine. For patients receiving ketoconazole, a 50% reduction in the initial tolterodine dosage is recommended.

Trimetrexate

In vitro data suggest that trimetrexate is extensively metabolized by CYP3A4. In vitro animal models have demonstrated that ketoconazole potently inhibits the metabolism of trimetrexate. Patients treated concomitantly with trimetrexate and ketoconazole tablets should be carefully monitored for trimetrexate-associated toxicities.

Verapamil

Findings of in vitro metabolic studies indicate that verapamil is metabolized by enzymes including CYP3A4. Ketoconazole may increase verapamil serum concentrations. Caution should be taken when co-administering verapamil with ketoconazole tablets.

Vinca Alkaloids (vincristine, vinblastine, vinorelbine)

Ketoconazole may inhibit the metabolism of vinca alkaloids metabolized by CYP3A4. Close monitoring for toxicities associated with vincristine, vinblastine, or vinorelbine is recommended when co-administered with ketoconazole tablets.

2. Effects of other drugs on ketoconazole

2.1 Drugs affecting the absorption of ketoconazole

Gastric Acid Suppressors/Neutralizers

Studies have shown that absorption of ketoconazole is impaired when gastric acid production is decreased. Reduced plasma concentrations of ketoconazole were reported when ketoconazole tablets were administered with antacids, antimuscarinics, histamine H2-blockers, proton pump inhibitors (omeprazole, lansoprazole) and sucralfate. (See PRECAUTIONS, Drug Interactions (General) section.)

2.2 Drugs that were shown or are expected to significantly reduce the systemic exposure to ketoconazole

Co-administration of ketoconazole with potent CYP3A4 enzyme inducers is not recommended.

Carbamazepine

Concomitant administration of ketoconazole tablets with carbamazepine may alter the metabolism of one or both of the drugs. Close monitoring for both plasma concentrations of carbamazepine and reduced ketoconazole efficacy is recommended.

Nevirapine

Ketoconazole AUC and Cmax decreased by a median of 63% and 40%, respectively, in HIV-infected patients who were given nevirapine 200 mg once daily for two weeks along with ketoconazole 400 mg daily. Concomitant administration of ketoconazole tablets and nevirapine is not recommended.

Phenytoin

Concomitant administration of ketoconazole with phenytoin may alter the metabolism of one or both of the drugs. Close monitoring for both plasma concentrations of phenytoin and reduced efficacy of ketoconazole tablets is recommended.

Rifampin, rifabutin, isoniazid

Concomitant administration of rifampin and rifabutin with ketoconazole tablets reduces the blood concentrations of the latter. INH (Isoniazid) was also reported to affect ketoconazole concentrations adversely. These antitubercular drugs should not be given concomitantly with ketoconazole tablets.

2.3 Drugs that significantly increase the systemic exposure to ketoconazole

Ritonavir

Concomitant administration of ritonavir with ketoconazole tablets increases was shown to increase the oral bioavailability of ketoconazole. Therefore, when ritonavir is to be given concomitantly, higher doses (>200 mg/day) of ketoconazole tablets should not be used.

3. Other drug interactions

Alcohol

Rare cases of a disulfiram-like reaction to alcohol have been reported. These experiences have been characterized by flushing, rash, peripheral edema, nausea, and headache. Symptoms resolved within a few hours.

Loratadine

After the co-administration of 200 mg oral ketoconazole twice daily and one 20 mg dose of loratadine to 11 subjects, the AUC and Cmax of loratadine averaged 302% (±142 S.D.) and 251% (± 68 S.D.), respectively, of those obtained after cotreatment with placebo. The AUC and Cmax of descarboethoxyloratadine, an active metabolite, averaged 155% (± 27 S.D.) and 141% (± 35 S.D.), respectively. However, no related changes were noted in the QTc on ECG taken at 2, 6, and 24 hours after the coadministration. Also, there were no clinically significant differences in adverse events when loratadine was administered with or without ketoconazole.

Carcinogenesis, Mutagenesis, Impairment of Fertility

Ketoconazole did not show any signs of mutagenic potential when evaluated using the dominant lethal mutation test or the Ames Salmonella microsomal activator assay. Ketoconazole was not carcinogenic in an 18-month, oral study in Swiss albino mice or a 24-month oral carcinogenicity study in Wistar rats at dose levels of 5, 20 and 80 mg/kg/ day. The high dose in these studies was approximately 1× (mouse) or 2× (rat) the clinical dose in humans based on a mg/m^2 comparison.

Pregnancy

Teratogenic effects

Pregnancy Category C

Ketoconazole has been shown to be teratogenic (syndactylia and oligodactylia) in the rat when given in the diet at 80 mg/kg/day (2 times the maximum recommended human dose, based on body surface area comparisons). However, these effects may be related to maternal toxicity, evidence of which also was seen at this and higher dose levels.

There are no adequate and well controlled studies in pregnant women. Ketoconazole tablets should be used during pregnancy only if the potential benefit justifies the potential risk to the fetus.

Nonteratogenic Effects

Ketoconazole has also been found to be embryotoxic in the rat when given in the diet at doses higher than 80 mg/kg during the first trimester of gestation.

In addition, dystocia (difficult labor) was noted in rats administered oral ketoconazole during the third trimester of gestation. This occurred when ketoconazole was administered at doses higher than 10 mg/kg (about one fourth the maximum human dose, based on body surface area comparison).

Nursing Mothers

Ketoconazole has been shown to be excreted in the milk. Mothers who are under treatment with ketoconazole tablets should not breast feed.

Pediatric Use

Ketoconazole tablets have not been systematically studied in children of any age, and essentially no information is available on children under 2 years. Ketoconazole tablets should not be used in pediatric patients unless the potential benefit outweighs the risks.

ADVERSE REACTIONS

Because clinical trials are conducted under widely varying conditions, adverse reaction rates observed in the clinical trials of a drug cannot be directly compared to rates in the clinical trials of another drug and may not reflect the rates observed in practice.

The following adverse reactions were reported in clinical trials:

Immune System Disorders: anaphylactoid reaction

Endocrine Disorders: gynecomastia

Metabolism and Nutrition Disorders: alcohol intolerance, anorexia, hyperlipidemia, increased appetite

Psychiatric Disorders: insomnia, nervousness

Nervous System Disorders: headache, dizziness, paresthesia, somnolence

Eye Disorders: photophobia

Vascular Disorders: orthostatic hypotension

Respiratory, Thoracic and Mediastinal Disorders: epistaxis

Gastrointestinal Disorders: vomiting, diarrhea, nausea, constipation, abdominal pain, abdominal pain upper, dry mouth, dysgeusia, dyspepsia, flatulence, tongue discoloration

Hepatobiliary Disorders: hepatitis, jaundice, hepatic function abnormal

Skin and Subcutaneous Tissues Disorders: erythema multiforme, rash, dermatitis, erythema, urticaria, pruritus, alopecia, xeroderma

Musculoskeletal and Connective Tissue Disorders: myalgia

Reproductive System and Breast Disorders: menstrual disorder

General Disorders and Administration Site Conditions: asthenia, fatigue, hot flush, malaise, edema peripheral, pyrexia, chills

Investigations: platelet count decreased.

Post-Marketing Experience

The following adverse reactions have been identified during postapproval use of ketoconazole tablets. Because these reactions are reported voluntarily from a population of uncertain size, it is not always possible to reliably estimate their frequency or establish a causal relationship to drug exposure.

The following adverse reactions were reported during post-marketing experience:

Blood and Lymphatic System Disorders: thrombocytopenia

Immune System Disorders: allergic conditions including anaphylactic shock, anaphylactic reaction, angioneurotic edema

Endocrine Disorders: adrenocortical insufficiency

Nervous System Disorders: reversible intracranial pressure increased (e.g. papilloedema, fontanelle bulging in infants)

Hepatobiliary Disorders: serious hepatotoxicity including hepatitis cholestatic, biopsyconfirmed hepatic necrosis, cirrhosis, hepatic failure including cases resulting in transplantation or death

Skin and Subcutaneous Tissue Disorders: acute generalized exanthematous pustulosis, photosensitivity

Musculoskeletal and Connective Tissue Disorders: arthralgia

Reproductive System and Breast Disorders: erectile dysfunction; with doses higher than the recommended therapeutic dose of 200 or 400mg daily, azoospermia.

OVERDOSAGE

In the event of acute accidental overdose, treatment consists of supportive and symptomatic measures. Within the first hour after ingestion, activated charcoal may be administered.

DOSAGE AND ADMINISTRATION

There should be laboratory as well as clinical documentation of infection prior to starting ketoconazole therapy. The usual duration of therapy for systemic infection is 6 months. Treatment should be continued until active fungal infection has subsided.

Adults

The recommended starting dose of ketoconazole tablets is a single daily administration of 200 mg (one tablet). If clinical responsiveness is insufficient within the expected time, the dose of ketoconazole tablets may be increased to 400 mg (two tablets) once daily.

Children

In small numbers of children over 2 years of age, a single daily dose of 3.3 to 6.6 mg/kg has been used. Ketoconazole tablets have not been studied in children under 2 years of age.

HOW SUPPLIED

Ketoconazole tablets USP, 200 mg are white to off-white round, flat tablets, one side scored and engraved with "T" above the score and "57" below the score. The other side is plain. They are supplied in bottles of 30 tablets (NDC 33261-0739-30).

STORAGE AND HANDLING

Store at 20°- 25°C (68°- 77°F) [See USP Controlled Room Temperature].

Protect from moisture.

Keep out of reach of children.

Mfd. by: Taro Pharmaceutical Industries Ltd., Haifa Bay, Israel 26110
Dist. by: Taro Pharmaceuticals U.S.A., Inc., Hawthorne, NY 10532

Repackaged By :
Aidarex Pharmaceuticals LLC,
Corona, CA 92880

Revised: August, 2013

79775-0813-3

MEDICATION GUIDE
Ketoconazole Tablets USP, 200 mg

What is the most important information I should know about ketoconazole tablets USP?

Ketoconazole tablets is not the only medicine available to treat fungal infections and should only be used when other medicines are not right for you. Talk to your healthcare provider to find out if ketoconazole tablets are right for you.

Ketoconazole tablets USP can cause serious side effects, including:

- liver problems (hepatotoxicity). Some people who were treated with ketoconazole the active ingredient in ketoconazole tablets, had serious liver problems that led to death or the need for a liver transplant. Call your healthcare provider right away if you have any of the following symptoms:
  - loss of appetite or start losing weight (anorexia)
  - nausea or vomiting
  - feel tired
  - stomach pain or tenderness
  - dark urine or light colored stools
  - yellowing of your skin or the whites of your eyes
  - fever or rash
- changes in the electrical activity of your heart called QT prolongation. QT prolongation can cause irregular heart beats that can be life threatening. This can happen when ketoconazole tablets are taken with certain medicines, such as dofetilide, quinidine, pimozide, and cisapride. Talk to your healthcare provider about other medicines you are taking before you start taking ketoconazole tablets. Tell your healthcare provider right away if you feel faint, lightheaded, dizzy, or feel your heart beating irregularly or fast. These may be symptoms related to QT prolongation.

What are ketoconazole tablets USP?

- Ketoconazole tablets are prescription medicine used to treat serious fungal infections including: blastomycosis, coccidioidomycosis, histoplasmosis, chromomycosis, and paracoccidioidomycosis.
- Ketoconazole tablets are not for people with fungal nail infections.
- Ketoconazole tablets have not been approved for the treatment of advanced prostate cancer or Cushing's syndrome. The safety and efficacy have not been established.
- Ketoconazole tablets should only be used in children if prescribed by the healthcare provider who has determined that the benefits outweigh the risks.

Who should not take ketoconazole tablets USP?

- Do not take ketoconazole tablets if you:
  - have liver problems
  - take simvastatin, and lovastatin. Ketoconazole tablets when taken with these medicines may cause muscle problems.
  - take eplerenone, dihydroergotamine, ergotamine, and nisoldipine.
  - take triazolam, midazolam, or alprazolam. Taking ketoconazole tablets with these medicines may make you very drowsy and make your drowsiness last longer.
  - are allergic to ketoconazole or any of the ingredients in ketoconazole tablets. See the end of this Medication Guide for a complete list of ingredients in ketoconazole tablets.

Before you take ketoconazole tablets USP, tell your healthcare provider if you:

- have had an abnormal heart rhythm tracing (ECG) or anyone in your family have or have had a heart problem called "congenital long QT syndrome".
- have adrenal insufficiency.
- are pregnant or plan to become pregnant. It is not known if ketoconazole tablets will harm your unborn baby.
- are breastfeeding or plan to breastfeed. Ketoconazole tablets can pass into your breast milk. You and your healthcare provider should decide if you will take ketoconazole tablets or breastfeed. You should NOT do both.

Tell your healthcare provider about all the medicines you take, including prescription and over-the-counter medicines, vitamins, and herbal supplements.

Using ketoconazole tablets with certain other medicines may affect each other. Using ketoconazole tablets with other medicines can cause serious side effects.

How should I take ketoconazole tablets USP?

- Take ketoconazole tablets 1 time each day.
- Do not stop taking ketoconazole tablets without first talking to your healthcare provider.

What should I avoid while taking ketoconazole tablets USP?

- Do not drink alcohol while taking ketoconazole tablets.

What are the possible side effects of ketoconazole tablets USP?

Ketoconazole tablets may cause serious side effects, including:

- See "What is the most important information I should know about ketoconazole tablets USP?"
- adrenal insufficiency. Adrenal insufficiency is a condition in which the adrenal glands do not make enough steroid hormones. Ketoconazole tablets may cause adrenal insufficiency if you take a high dose. Your healthcare provider will follow you closely if you have adrenal insufficiency or if you are taking prednisone or other similar medicines for long periods of time. Call your healthcare provider right away if you have symptoms of adrenal insufficiency such as tiredness, weakness, dizziness, nausea, and vomiting.
- serious allergic reactions. Some people can have a serious allergic reaction to ketoconazole tablets. Stop taking ketoconazole tablets and go to the nearest hospital emergency room right away if you get a rash, itching, hives, fever, swelling of the lips or tongue, chest pain, or have trouble breathing. These could be signs of a serious allergic reaction.
- muscle problems. Taking certain medicines with ketoconazole tablets may cause muscle problems. See "Who should not take ketoconazole tablets USP?"

The most common side effects of ketoconazole tablets include nausea, headache, diarrhea, stomach pain, and abnormal liver function tests.

These are not all the possible side effects of ketoconazole tablets. For more information, ask your healthcare provider or pharmacist.

Call your doctor for medical advice about side effects. You may report side effects to FDA at 1-800-FDA-1088.

How should I store ketoconazole tablets USP?

- Store ketoconazole tablets at room temperature between 68°F to 77°F (20°C to 25°C).
- Keep ketoconazole tablets dry.

General information about the safe and effective use of ketoconazole tablets USP.

Medications are sometimes prescribed for purposes other than those listed in a Medication Guide. Do not use ketoconazole tablets for a condition for which it was not prescribed. Do not give ketoconazole tablets to other people, even if they have the same symptoms that you have. It may harm them.

This Medication Guide summarizes the most important information about ketoconazole tablets.

If you would like more information, talk to your healthcare provider. You can ask your pharmacist or healthcare provider for information about ketoconazole tablets that is written for health professionals.

What are the ingredients in ketoconazole tablets USP, 200 mg?

Active ingredient: ketoconazole.

Inactive ingredients: colloidal silicon dioxide, corn starch, lactose monohydrate, magnesium stearate, microcrystalline cellulose, and povidone.

This Medication Guide has been approved by the U.S. Food and Drug Administration

Mfd. by: Taro Pharmaceutical Industries Ltd., Haifa Bay, Israel 26110
Dist. by: Taro Pharmaceuticals U.S.A., Inc., Hawthorne, NY 10532

Repackaged By :
Aidarex Pharmaceuticals LLC,
Corona, CA 92880

Revised: August, 2013

79775-0813-3

PRINCIPAL DISPLAY PANEL - 200 mg Tablet Bottle Label

NDC 33261-0739-30

30 Tablets

Ketoconazole
Tablets, USP
200 mg

DISPENSE THE ACCOMPANYING
MEDICATION GUIDE TO EACH PATIENT.

Rx only